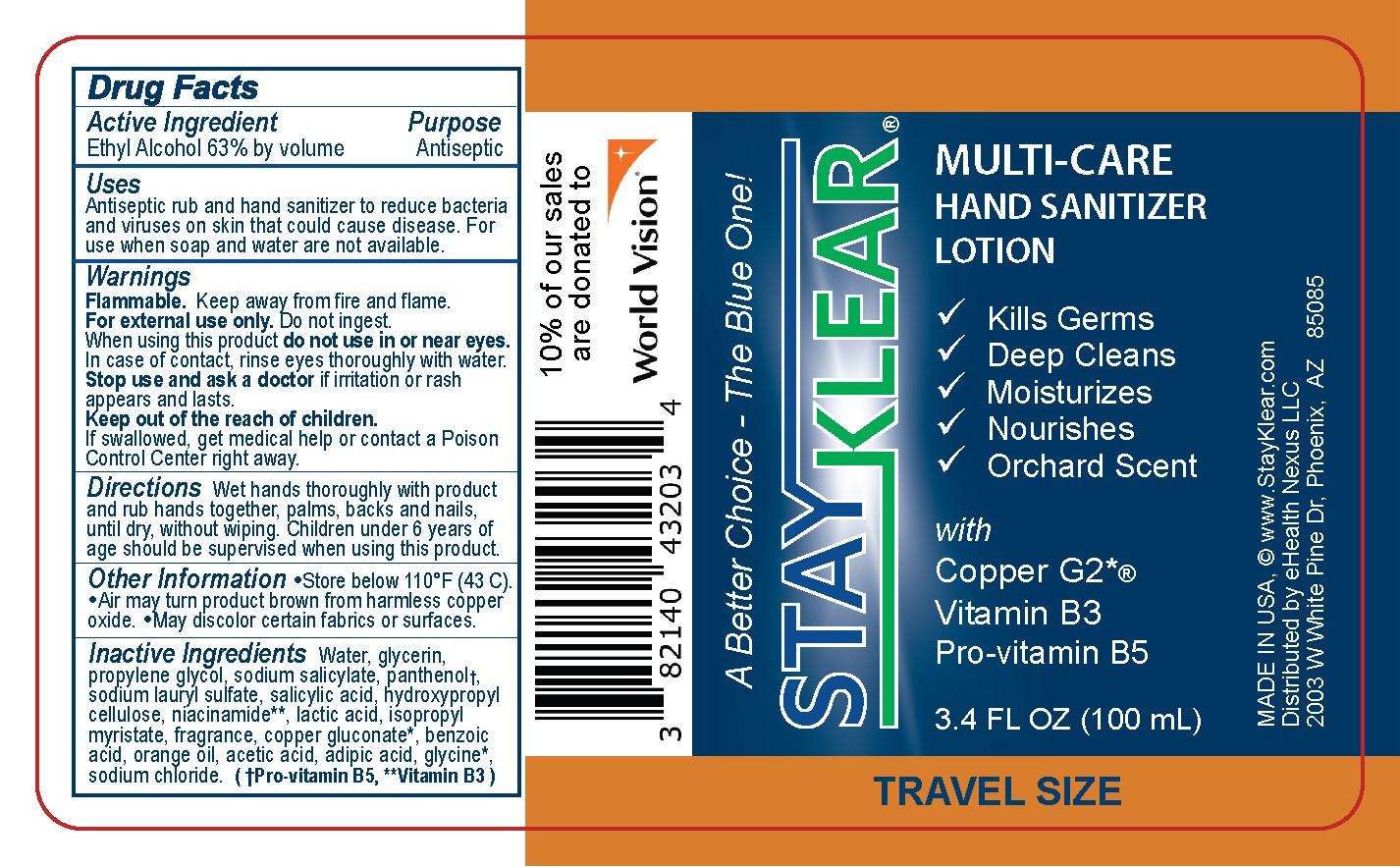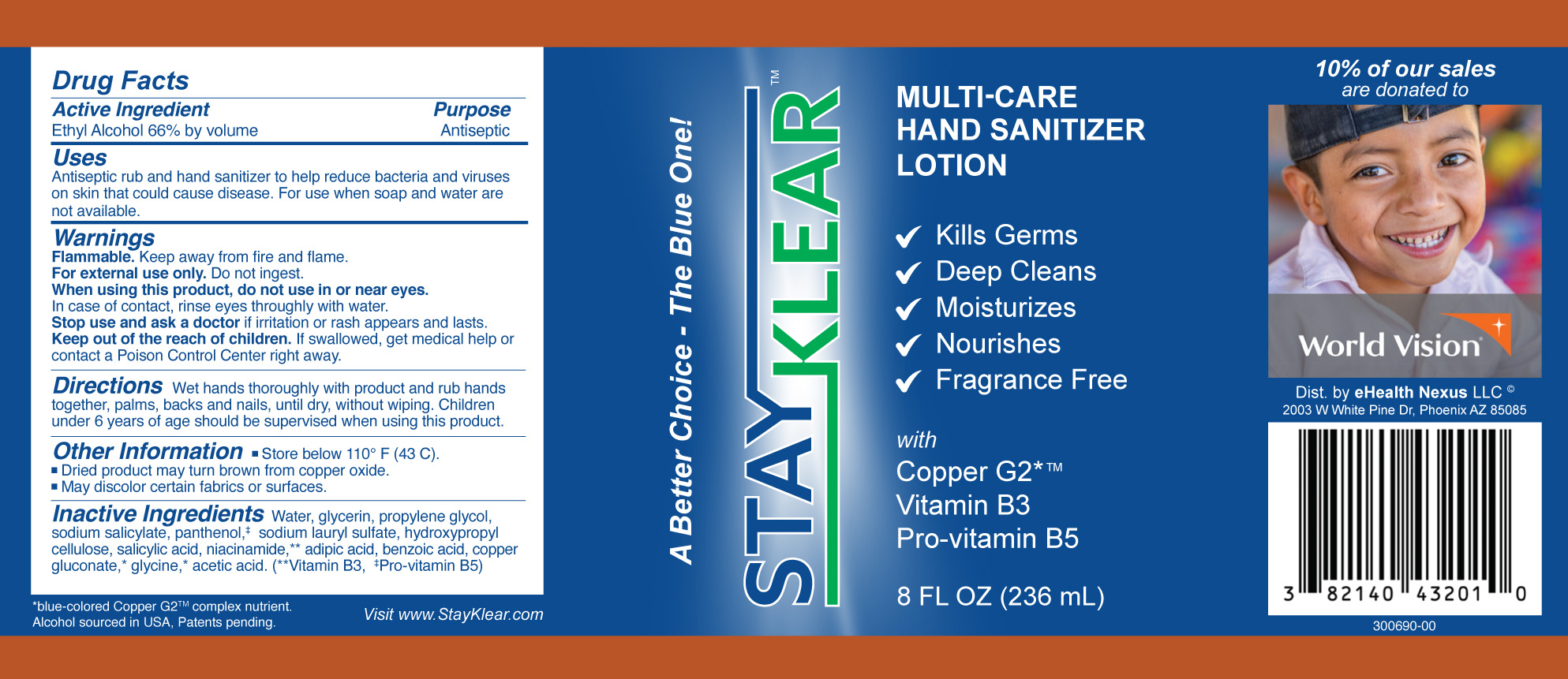 DRUG LABEL: STAYKLEAR
NDC: 82140-432 | Form: LIQUID
Manufacturer: eHealth Nexus LLC
Category: otc | Type: HUMAN OTC DRUG LABEL
Date: 20240624

ACTIVE INGREDIENTS: ALCOHOL 0.6 kg/1 kg
INACTIVE INGREDIENTS: VANILLIN 0.001 kg/1 kg; BENZYL BENZOATE 0.001 kg/1 kg; ISOPROPYL MYRISTATE 0.003 kg/1 kg; LACTIC ACID 0.003 kg/1 kg; WATER 0.29 kg/1 kg; HYDROXYPROPYL CELLULOSE, UNSPECIFIED 0.0055 kg/1 kg; PANTHENOL 0.008 kg/1 kg; PROPYLENE GLYCOL 0.016 kg/1 kg; SODIUM SALICYLATE 0.008 kg/1 kg; GLYCERIN 0.034 kg/1 kg; SODIUM LAURYL SULFATE 0.006 kg/1 kg; NIACINAMIDE 0.0032 kg/1 kg; ADIPIC ACID 0.0015 kg/1 kg; BENZOIC ACID 0.002 kg/1 kg; SALICYLIC ACID 0.006 kg/1 kg; GLYCINE 0.001 kg/1 kg; COPPER GLUCONATE 0.0022 kg/1 kg; ACETIC ACID 0.0013 kg/1 kg; SODIUM CHLORIDE 0.0006 kg/1 kg; ORANGE OIL 0.0015 kg/1 kg

Active Ingredient

Ethyl Alcohol 63% by volume

Purpose

Antiseptic

Uses

Antiseptic rub and hand sanitizer to help reduce bacteria and viruses on skin that could cause disease. For use when soap and water are not available.

Warnings:

Flammable. Keep away from fire and flame.

For external use only. Do not ingest.

When using this product, do not use in or near eyes.

In case of contact, rinse eyes thoroughly with water.

Stop use and ask a doctor, if irritation or rash appears and lasts.

KEEP OUT OF REACH OF CHILDREN

Keep out of the reach of children. If swallowed, get medical help or contact a Poison Control Center right away.

Directions:

Wet hands thoroughly with product and rub hands together, palms, backs and nails and wrists, until dry, without wiping. Children under 6 years of age should be supervised when using this product.

Directions

Wet hands thoroughly with product and rub hands together, palms, backs and nails, until dry, without wiping. Children under 6 years of age should be supervised when using this product.

Other Information:

Store below 110° F (43 C).

•Dried product may turn brown from copper oxide.
•May discolor certain fabrics or surfaces.

Inactive Ingredients:

Water, glycerin, propylene glycol, sodium salicylate, panthenol,‡ sodium lauryl sulfate, salicylic acid, hydroxypropyl cellulose, lactic acid, niacinamide,** isopropyl myristate, fragrance, copper gluconate, benzoic acid, orange oil, adipic acid, acetic acid, glycine, sodium chloride. **Vitamin B3, ‡Pro-vitamin B5